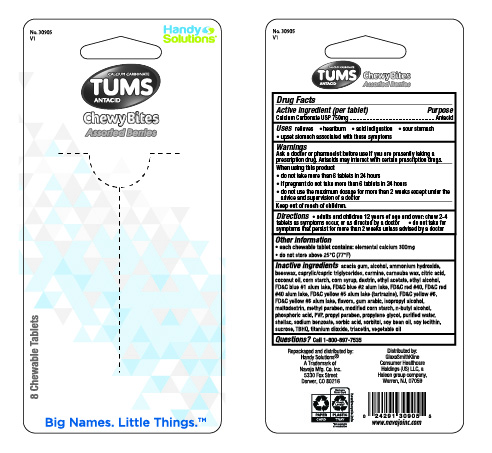 DRUG LABEL: Tums Chewy Bites Assorted Berries
NDC: 67751-227 | Form: TABLET, CHEWABLE
Manufacturer: Navajo Manufacturing Company Inc.
Category: otc | Type: HUMAN OTC DRUG LABEL
Date: 20240415

ACTIVE INGREDIENTS: CALCIUM CARBONATE 750 mg/1 1
INACTIVE INGREDIENTS: ACACIA; ALCOHOL; AMMONIA; YELLOW WAX; MEDIUM-CHAIN TRIGLYCERIDES; CARMINIC ACID; CARNAUBA WAX; CITRIC ACID MONOHYDRATE; COCONUT OIL; STARCH, CORN; CORN SYRUP; ICODEXTRIN; ETHYL ACETATE; FD&C BLUE NO. 1; ALUMINUM OXIDE; FD&C BLUE NO. 2; FD&C RED NO. 40; FD&C YELLOW NO. 5; FD&C YELLOW NO. 6; ISOPROPYL ALCOHOL; MALTODEXTRIN; METHYLPARABEN; MODIFIED CORN STARCH (1-OCTENYL SUCCINIC ANHYDRIDE); BUTYL ALCOHOL; PHOSPHORIC ACID; POVIDONE, UNSPECIFIED; PROPYLPARABEN; PROPYLENE GLYCOL; WATER; SHELLAC; SODIUM BENZOATE; SORBIC ACID; SORBITOL; SOYBEAN OIL; LECITHIN, SOYBEAN; SUCROSE; TERT-BUTYLHYDROQUINONE; TITANIUM DIOXIDE; TRIACETIN

CARDED TUMS CHEWY BITES ASSORTED BERRIES 8CT BOTTLE

Active ingredient (per tablet)

Calcium Carbonate USP 750mg

Purpose

Antacid

Uses

relieves

- heartburn
- acid indigestion
- sour stomach
- upset stomach associated with these symptoms

Warnings

Ask a doctor or pharmacist before use if you are

presently taking a prescription drug. Antacids may interact with certain prescription drugs.

When using this product

- do not take more than 6 tablets in 24 hours
- if pregnant do not take more than 6 tablets in 24 hours
- do not use the maximum dosage for more than 2 weeks except under the advice and supervision of a doctor

Directions

- adults and children 12 years of age and over:chew 2-4 tablets as symptoms occur, or as directed by a doctor
- do not take for symptoms that persist for more than 2 weeks unless advised by a doctor

Other Information

- each chewable tablet contains:elemental calcium 300mg
- do not store above 25°C (77°F)

Inactive ingredients

acacia gum, alcohol, ammonium hydroxide, beeswax, caprylic/capric triglycerides, carmine, carnauba wax, citric acid, coconut oil, corn starch, corn syrup, dextrin, ethyl acetate, ethyl alcohol, FD&C blue #1 alum lake, FD&C blue #2 alum lake, FD&C red #40, FD&C red #40 alum lake, FD&C yellow #5 alum lake (tartrazine), FD&C yellow #6, FD&C yellow #6 alum lake, flavors, gum arabic, isopropyl alcohol, maltodextrin, methyl paraben, modified corn starch, n-butyl alcohol, phosphoric acid, PVP, propyl paraben, propylene glycol, purified water, shellac, sodium benzoate, sorbic acid, sorbitol, soy bean oil, soy lecithin, sucrose, TBHQ, titanium dioxide, triacetin, vegetable oil

Questions?

Call 1-800-897-7535